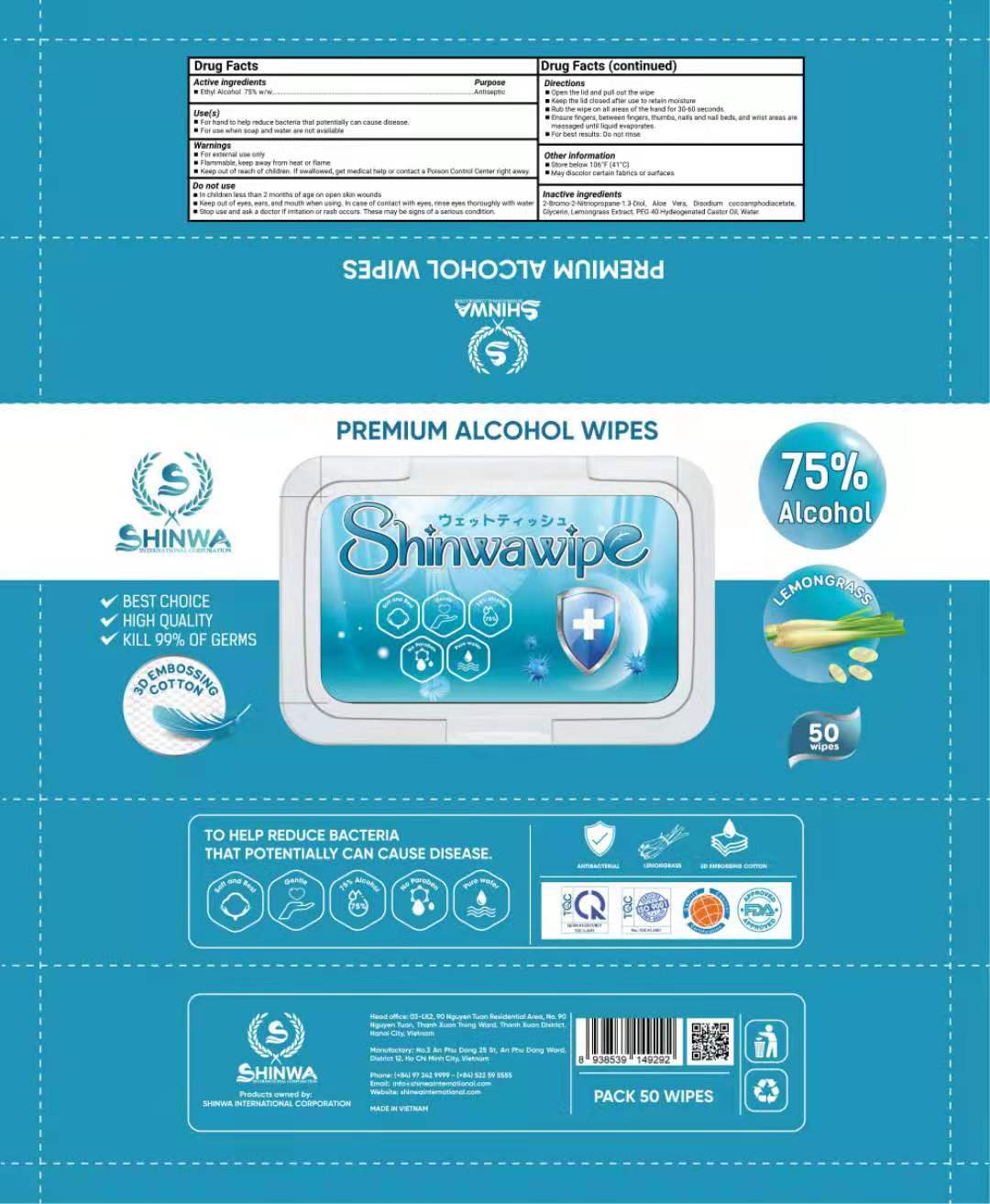 DRUG LABEL: PREMIUM ALCOHOL WIPES
NDC: 81889-301 | Form: CLOTH
Manufacturer: SHINWA INTERNATIONAL CORPORATION
Category: otc | Type: HUMAN OTC DRUG LABEL
Date: 20210511

ACTIVE INGREDIENTS: ALCOHOL 75 1/100 1
INACTIVE INGREDIENTS: WEST INDIAN LEMONGRASS OIL; DISODIUM COCOAMPHODIACETATE; BRONOPOL; GLYCERIN; POLYOXYL 40 HYDROGENATED CASTOR OIL; ALOE VERA LEAF; WATER

PREMIUM ALCOHOL WIPES

PREMIUM ALCOHOL WIPES

Active Ingredient(s)

ETHYL ALCOHOL 75%. Purpose: Antiseptic

Purpose

Antiseptic, PREMIUM ALCOHOL WIPES

Use

PREMIUM ALCOHOL WIPES to help reduce bacteria that potentially can cause disease. For use when soap and water are not available.

Warnings

For external use only. Flammable. Keep away from heat or flame

Do not use

- in children less than 2 months of age
- on open skin wounds

When using this product keep out of eyes, ears, and mouth. In case of contact with eyes, rinse eyes thoroughly with water.
Stop use and ask a doctor if irritation or rash occurs. These may be signs of a serious condition.
Keep out of reach of children. If swallowed, get medical help or contact a Poison Control Center right away.

Stop use and ask a doctor if irritation or rash occurs. These may be signs of a serious condition.

Keep out of reach of children. If swallowed, get medical help or contact a Poison Control Center right away.

Directions

- Wipe the skin and let it dry naturally.
- Supervise children under 6 years of age when using this product to avoid swallowing.

Other information

- Store between 15-30C (59-86F)
- Avoid freezing and excessive heat above 40C (104F)

Inactive ingredients

WATER
GLYCERIN
ALOE VERA
LEMONGRASS EXTRACT
DISODIUM COCOAMPHODIACETATE
2-BROMO-2-NITROPROPANE 1.3-DIOL
PEG 40 HYDROGENATED CASTOR OIL